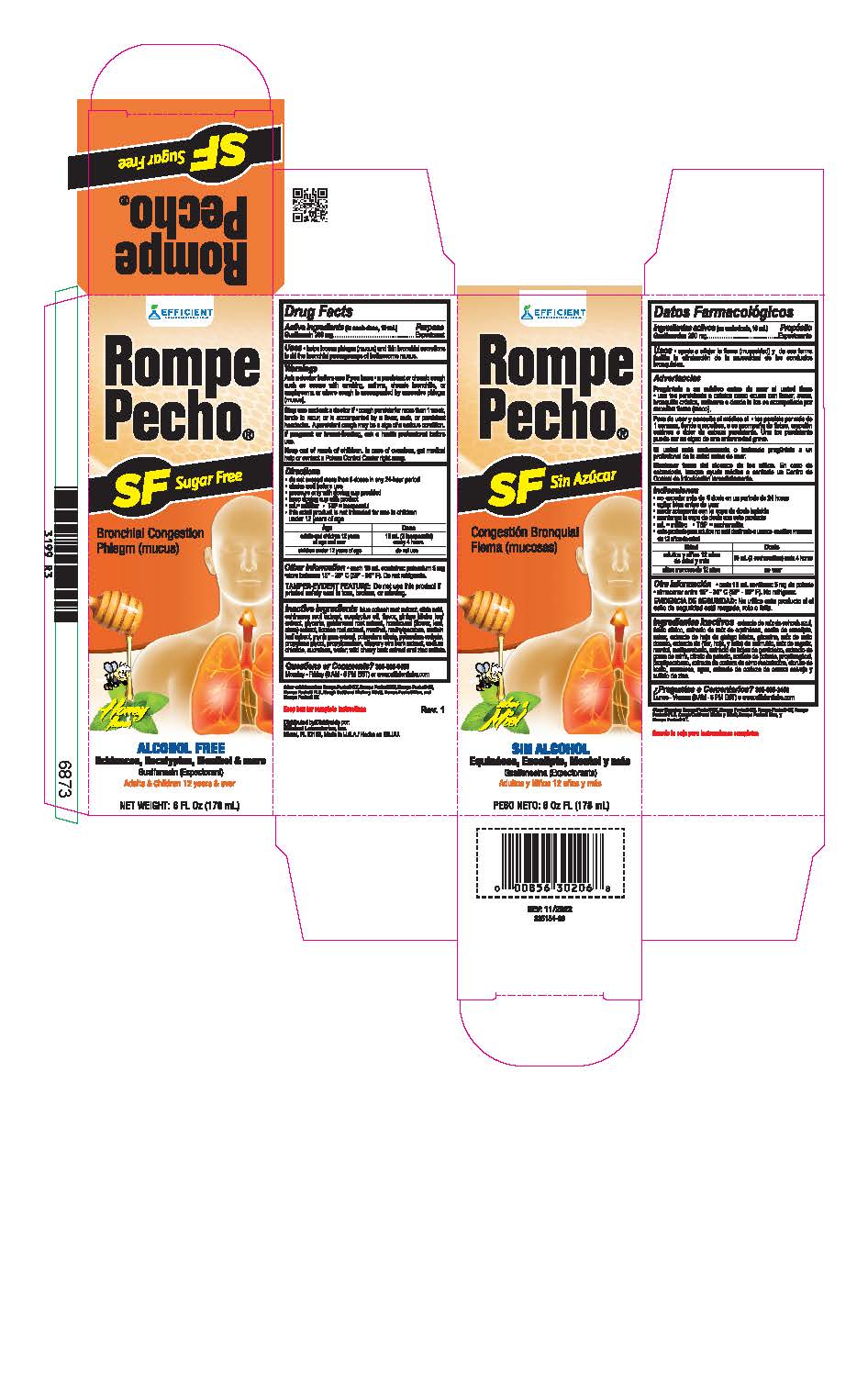 DRUG LABEL: Rompe Pecho
NDC: 58593-265 | Form: LIQUID
Manufacturer: Efficient Laboratories, Inc.
Category: otc | Type: HUMAN OTC DRUG LABEL
Date: 20251014

ACTIVE INGREDIENTS: GUAIFENESIN 100 mg/5 mL
INACTIVE INGREDIENTS: SUCRALOSE; CAULOPHYLLUM THALICTROIDES ROOT; CITRIC ACID MONOHYDRATE; ECHINACEA, UNSPECIFIED; EUCALYPTUS OIL; GINKGO; GLYCERIN; GOLDENSEAL; HOREHOUND; GLYCYRRHIZA GLABRA; MENTHOL; METHYLPARABEN; VERBASCUM DENSIFLORUM LEAF; MYRRH; POTASSIUM CITRATE; POTASSIUM SORBATE; PROPYLENE GLYCOL; PROPYLPARABEN; WATER; ULMUS RUBRA BARK; SODIUM CHLORIDE; ZINC SULFATE; PRUNUS SEROTINA BARK

Drug Facts

Active Ingredient (In each 5ml teaspoonful)................. Purpose
Guaifenesin 100 mg ...................................................... Expectorant

Purpose

Expectorant

Uses
• Helps loosen phlegm (mucus) and thin bronchial secretions to rid the bronchial passageways of bothersome
mucus

Warnings
Do not exceed recommended dosage.

Ask a doctor before use if you have

- a persistent or chronic cough such as occurs with smoking, asthma, chronic bronchitis, or emphysema or where cough is accompanied by excessive phlegm (mucus)

Stop use and ask a doctor if
• cough persists for more than 1 week, tends to recur, or is accompainied by a fever, rash or persistent headache. A persistent cough may be a sign of serious condition.

Keep out of reach of children.
In case of accidental overdose, get medical help or contact the Poison Control Center right away.

PREGNANCY OR BREAST FEEDING

If pregnant or breast-feeding, ask a health professional before use.

DOSAGE AND ADMINISTRATION

Directions:Shake well before use. Do not exceed 6 doses in any 24 hour period or as directed by a doctor

Age | Dose
adults and children 12 years of age and over | 10 mL (2tsps) every 4 hours
children 6 to under 12 years of age | 5 mL (1 tsp) every 4 hours
children under 6 years of age | consult a doctor

Inactive Ingredients:

Blue Cohosh root extract, Citric Acid, Echinacea root extract, Eucalyptus Oil, Ginkgo Biloba leaf extract, Glycerin, Golden Seal Root extract, Honey Flavor, Horehound, Licorice Root extract, Menthol, Methylparaben, Mullein Leaf extract, Myrrh gum extract, Potassium Citrate, Potassium Sorbate, Propylene Glycol, Propylparaben, Slippery Elm Bark extract, Sodium Chloride, Sucralose, Water, Wild Cherry Bark extract and Zinc Sulfate.

Questions or Comments?

305-805-3456 Monday-Friday 9AM-5PM EST

www.efficientlabs.com